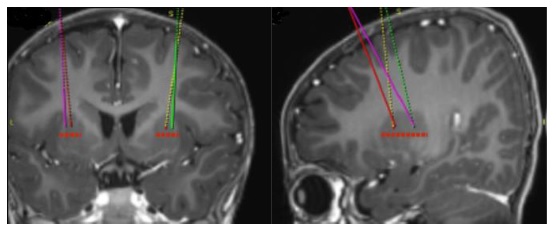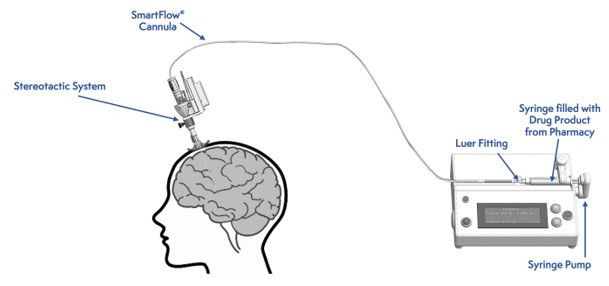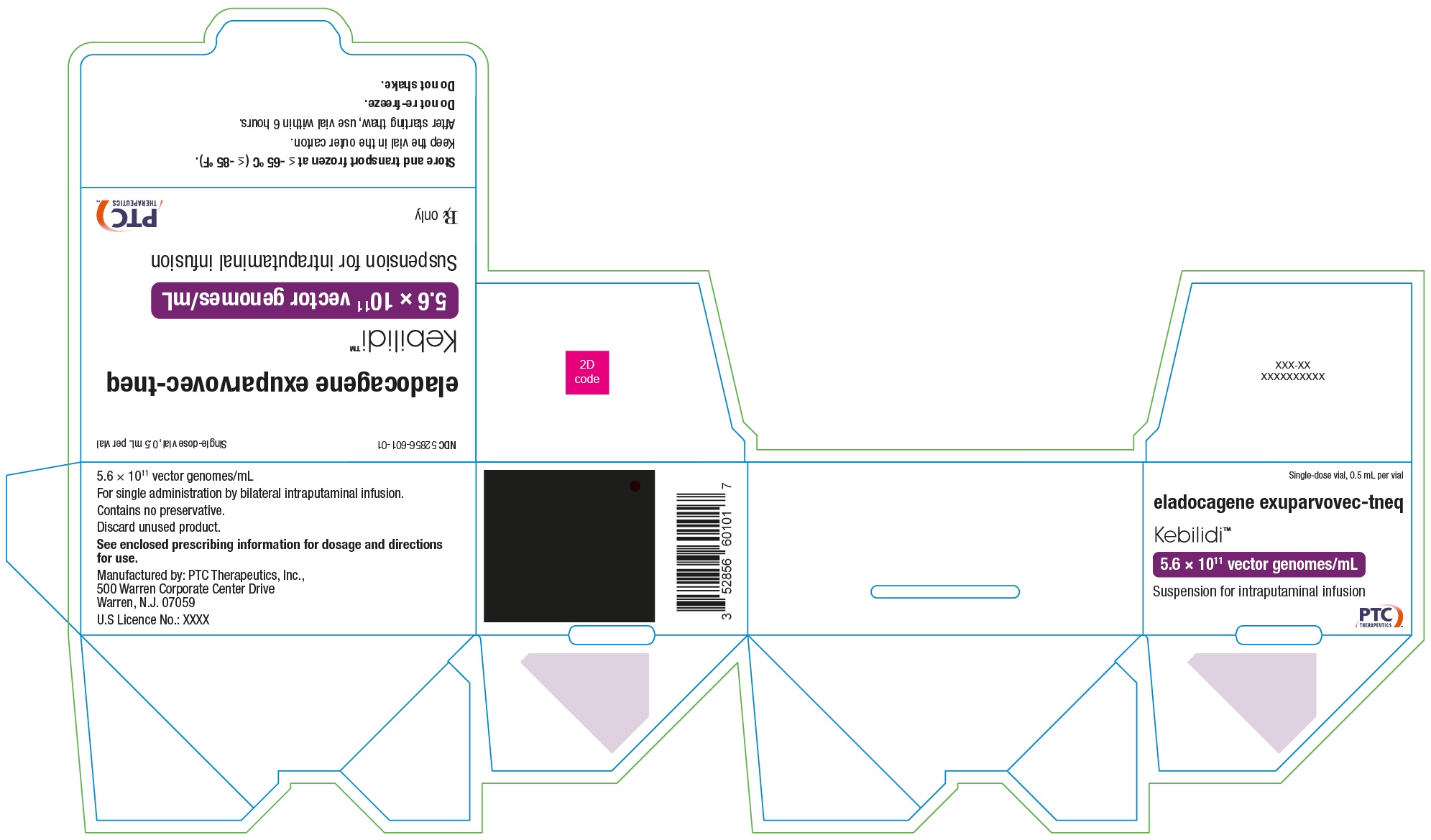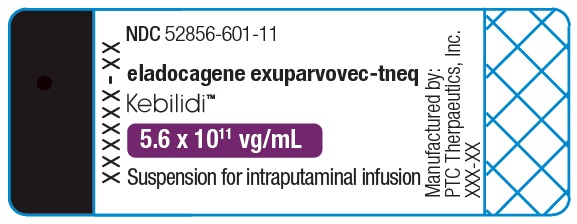 DRUG LABEL: KEBILIDI
NDC: 52856-601 | Form: SUSPENSION
Manufacturer: PTC Therapeutics, Inc.
Category: prescription | Type: HUMAN PRESCRIPTION DRUG LABEL
Date: 20260113

ACTIVE INGREDIENTS: ELADOCAGENE EXUPARVOVEC 560000000000 {GC}/1 mL
INACTIVE INGREDIENTS: POTASSIUM CHLORIDE; SODIUM CHLORIDE; MONOBASIC POTASSIUM PHOSPHATE; SODIUM PHOSPHATE, DIBASIC, ANHYDROUS; POLOXAMER 188; WATER

HIGHLIGHTS OF PRESCRIBING INFORMATION

These highlights do not include all the information needed to use KEBILIDI safely and effectively. See full prescribing information for KEBILIDI.
KEBILIDI (eladocagene exuparvovec-tneq) suspension, for intraputaminal infusion
Initial U.S. Approval: 2024

1 INDICATIONS AND USAGE

KEBILIDI is an adeno-associated virus (AAV) vector-based gene therapy indicated for the treatment of adult and pediatric patients with aromatic L amino acid decarboxylase (AADC) deficiency.

This indication is approved under accelerated approval based on change from baseline in gross motor milestone achievement at 48 weeks post-treatment. Continued approval for this indication may be contingent upon verification and description of clinical benefit in a confirmatory clinical trial. (1, 14)

2 DOSAGE AND ADMINISTRATION

For single-dose intraputaminal infusion only.

- Recommended dose: 1.8×10^11 vector genomes (vg). (2.2)
- Brain imaging for stereotactic planning and intraoperative navigation should be done prior to the procedure. (2.4)
- Post stereotactic registration, mark the entry point on the skull. Surgical access through the skull bone and dura should be performed. (2.4)
- Administer a total dose of 1.8×10^11 vg (0.32 mL total volume) delivered as four 0.08 mL (0.45×10^11 vg) infusions (two sites per putamen-anterior and posterior) at a rate of 0.003 mL/minute (0.18 mL/hour) for a total of 27 minutes per site, administered in a single stereotactic surgery using a cannula that is FDA-authorized for intraparenchymal infusion. (2.2, 2.4)

3 DOSAGE FORMS AND STRENGTHS

- KEBILIDI is a suspension for intraputaminal administration with a nominal concentration of 5.6×10^11 vg/mL. (3)
- KEBILIDI is supplied in a single-dose vial that contains 2.8×10^11 vg of eladocagene exuparvovec-tneq in an extractable volume of 0.5 mL of suspension. Each mL of suspension contains 5.6×10^11 vg of eladocagene exuparvovec-tneq. (3, 16)

4 CONTRAINDICATIONS

- Patients who have not achieved skull maturity assessed by neuroimaging. (4)

5 WARNINGS AND PRECAUTIONS

- Procedural complications: Monitor patients for procedural complications for neurosurgery, including events of respiratory and cardiac arrest after administration of KEBILIDI. (5.1)
- Dyskinesia: Monitor patients for dyskinesia after treatment with KEBILIDI. The use of dopamine antagonists can be used to control dyskinesia symptoms. (5.2)

6 ADVERSE REACTIONS

Most common adverse reactions (incidence ≥15%) were dyskinesia, pyrexia, hypotension, anemia, salivary hypersecretion, hypokalemia, hypophosphatemia, insomnia, hypomagnesemia, and procedural complications. (6.1)

To report SUSPECTED ADVERSE REACTIONS, contact PTC Therapeutics, Inc at toll-free phone 1 866 562 4620 or FDA at 1-800-FDA-1088 or www.fda.gov/medwatch.

FULL PRESCRIBING INFORMATION

1 INDICATIONS AND USAGE

KEBILIDI (eladocagene exuparvovec-tneq) is an adeno-associated virus (AAV) vector-based gene therapy indicated for the treatment of adult and pediatric patients with aromatic L-amino acid decarboxylase (AADC) deficiency.

This indication is approved under accelerated approval based on the change from baseline in gross motor milestone achievement at 48 weeks post treatment [see Clinical Studies (14)]. Continued approval for this indication may be contingent upon verification and description of clinical benefit in a confirmatory clinical trial.

2 DOSAGE AND ADMINISTRATION

For single-dose intraputaminal infusion only.

2.1 Important Dosing Information

- Confirm patient has AADC deficiency due to biallelic mutations in the DDC gene.
- Strictly observe aseptic technique during preparation and administration of KEBILIDI.
- KEBILIDI should be administered in a medical center which specializes in stereotactic neurosurgery.
- Administer KEBILIDI only using an FDA-authorized cannula for intraparenchymal infusion (i.e., ClearPoint SmartFlow Neuro Cannula Part Number NGS-NC-01-EE or NGS-NC-02-EE).
- Use of the syringe (i.e., connecting the syringe to the syringe pump and priming of the cannula) should begin within 6 hours of starting product thaw
- KEBILIDI is intended to be administered with an infusion pump capable of infusing at a rate of 0.003 mL/min.

2.2 Recommended Dose

KEBILIDI is administered as four intraputaminal infusions in a single stereotactic neurosurgical procedure as per the recommended dose shown in Table 1.

Table 1: Recommended Dose of KEBILIDI

Total Recommended Dose | 1.8x10^11 vg (0.32 mL)
Total number of infusions | 4
Volume (dose) per infusion | 0.08 mL (0.45x10^11 vg)
Location of infusions | 2 in anterior putamen, 2 in posterior putamen
Infusion rate at each target point | 0.003 mL/min
Dose duration for infusion at each target point | 27 minutes

2.3 Preparation

Thawing KEBILIDI Vial

- Coordinate timing of KEBILIDI thaw and infusion. KEBILIDI should be used within 6 hours of starting product thaw. Infusion of KEBILIDI takes 4 hours. The maximum time from thaw to completion of infusion should be no more than 10 hours.
- Thaw the KEBILIDI vial upright at room temperature before use. The contents of the vial will thaw in approximately 15 minutes at room temperature. Do not thaw or warm the vial any other way. Gently invert the vial 3 times. Do not shake the vial.
- Inspect the fully thawed KEBILIDI vial after mixing. KEBILIDI should be inspected visually for particulate matter, and discoloration prior to administration. KEBILIDI is clear to slightly opaque. The color of KEBILIDI should be a colorless to faint white suspension
- Do not use if particulates, or discoloration are visible in the suspension.

Preparing KEBILIDI in Syringe

1. Gather supplies listed in Table 2 for preparation:
  Table 2: Supplies for KEBILIDI Preparation
  Component | Material of Construction
  1mL lubricated sterile Luer-lock syringe with elastomer plunger Or 5mL lubricated sterile Luer-lock syringe with elastomer plunger | Silicone, PC; Silicone, PP Silicone, PP
  18 or 19 G sterile needle with 5µm filter | Stainless steel, PC hub; Stainless steel, PP hub
  Sterile Luer-lock syringe cap | -
  Plastic bag for delivery into surgical unit | -
  Secondary container for delivery into surgical unit | -
  Abbreviations: PC=Polycarbonate; PP=Polypropylene
2. Prepare KEBILIDI using sterile techniques under aseptic conditions, proper engineering controls (e.g., biological safety cabinets or isolator) as per the institutional policies.
3. Open the syringe and label it as the product-filled syringe.
4. Attach the filter needle to the syringe.
5. Draw the full volume of the vial of KEBILIDI into the syringe. Invert the vial and syringe and partially withdraw or angle the needle as necessary to maximize recovery of product.
6. Draw air into the syringe so that the needle is emptied of product. Carefully remove the needle from syringe containing KEBILIDI. Purge the air from the syringe until there is no air bubble and then cap with a syringe cap.
7. Place the syringe in a plastic bag and seal the bag.
8. Place the plastic bag in an appropriate secondary container for delivery to the surgical suite at room temperature.
9. The filled syringe prepared under aseptic conditions for delivery to the surgical site should be used immediately.

Notes:

- Do not refreeze thawed product.
- Dispose any remaining KEBILIDI or disposable material in compliance with institutional policy

2.4 Administration

Gather supplies for administration:
- KEBILIDI [see How Supplied/Storage and Handling (16)]
- SmartFlow Neuro Cannula
- Syringe pump, capable of an infusion rate of 0.003 mL/min and compatible with 1 mL or 5 mL syringe sizes
- Stereotactic system

Identification of the Target Points Within the Putamen

- Using standard neurosurgical stereotactic procedure, brain imaging for stereotactic planning and intraoperative navigation should be done prior to the procedure (see Figure 1).
  Figure 1: Four Target Points within the Putamen for Infusion Sites
- After stereotactic registration is complete, mark the entry point on the skull. Surgical access through the skull bone and dura should be performed.
  Figure 2: Infusion Delivery System

Intraputaminal Administration of KEBILIDI

Administer KEBILIDI by bilateral intraputaminal infusion using a single infusion cannula in one surgical session at two sites (anterior and posterior) per putamen. The infusion cannula is placed and infusion performed separately for each target point (see Figure 2).

1. Tightly connect the syringe containing the prepared KEBILIDI to Luer Lock connector at the proximal end of the infusion cannula.
2. Load syringe onto the infusion pump and secure appropriately.
3. Set infusion pump occlusion limit to the highest level to prevent pump from alarming or disrupting the infusion.
4. Prime KEBILIDI at the rate of up to 0.003 mL/minute (0.18 mL/hour) until the first drop of the product can be seen at the tip of the needle.
5. Place sterile absorbent pad or gauze under the tip of the cannula to contain drops of the prepared product that might emerge during priming.
6. Run the infusion pump prior to insertion of the cannula to ensure the prepared product is flowing from the tip immediately before insertion.
7. Place the infusion SmartFlow Neuro Cannula at the designation point in the putamen using stereotactic tools based on pre-planned stereotactic trajectories.
8. Starting with the first target site, insert the cannula through a burr hole into the putamen and then incrementally withdraw cannula along the intraputaminal infusion track, distributing the 0.08 mL (infused at a rate of 0.003 mL/min) of KEBILIDI per putamen across the planned trajectory to optimize distribution across the target site. The pump should run continuously throughout the 27-minute infusion, including during the repositioning to the designated sites along the infusion track.
9. Once the infusion is complete, stop the pump and leave the cannula in place for 5 minutes before withdrawing. Re-zero the total delivered volume setting on the infusion pump as soon as the cannula is inserted to the target and perform infusion. Reinsert at the next target point, repeating the same procedure for the other 3 target points.
10. After standard neurosurgical closure procedures, carry out a postoperative brain imaging examination of the patient to ensure there are no complications (e.g., bleeding).

3 DOSAGE FORMS AND STRENGTHS

KEBILIDI is a sterile suspension for intraputaminal infusion. Each single-dose vial contains 2.8×10^11 vg/0.5 mL (nominal concentration of 5.6×10^11 vg/mL) of KEBILIDI and each 2 mL vial contains an extractable volume of 0.5 mL.

Following product thaw, the suspension for infusion is a clear to slightly opaque, colorless to faint white liquid, free of visible particulates [see How Supplied/Storage and Handling (16)].

4 CONTRAINDICATIONS

KEBILIDI is contraindicated in patients who have not achieved skull maturity assessed by neuroimaging. Skull maturity is needed for stereotactic neurosurgical administration of KEBILIDI.

5 WARNINGS AND PRECAUTIONS

5.1 Procedural Complications

Procedural complications have been reported after neurosurgery required for KEBILIDI administration. These events included respiratory and cardiac arrest which occurred within 24 hours of the neurosurgical procedure and during post-surgical care [see Adverse Reactions (6)]. KEBILIDI administration has the potential risk for additional procedure related adverse events including cerebrospinal fluid (CSF) leak, intracranial bleeding, neuroinflammation, acute infarction, and infection.

Monitor patients for procedure related adverse events with KEBILIDI administration, including continuous cardiorespiratory monitoring during hospitalization.

5.2 Dyskinesia

Dyskinesia was reported after administration of KEBILIDI. All events were reported within 3 months of administration and 2 events required hospitalization [see Adverse Reactions (6)].

Monitor patients for signs and symptoms of dyskinesia after KEBILIDI treatment which may include involuntary movements of face, arm, leg, or entire body. These may present as fidgeting, writhing, wriggling, head bobbing or body swaying. The use of dopamine antagonists may be considered to control dyskinesia symptoms.

6 ADVERSE REACTIONS

6.1 Clinical Trials Experience

Because clinical trials are conducted under widely varying conditions, adverse reaction rates observed in the clinical trials of a drug cannot be directly compared to rates in the clinical trials of another drug and may not reflect the rates observed in practice.

The safety data described in this section reflects exposure to KEBILIDI in 13 pediatric patients with genetically confirmed AADC deficiency who received a single dose of 1.8×10^11 vg. The median duration of follow-up was 72 weeks (range 23 to 109 weeks) [see Clinical Studies (14)].

The most common adverse reactions (incidence ≥15%) are summarized in Table 3.

Table 3: Adverse Reactions in ≥15% of Patients in Study 1

Adverse Reaction | Patients Treated with KEBILIDI N=13 (%)
Dyskinesia | 10 (77%)
Pyrexia | 5 (38%)
Hypotension | 4 (31%)
Anemia | 4 (31%)
Salivary hypersecretion | 3 (23%)
Hypokalemia | 3 (23%)
Hypophosphatemia | 3 (23%)
Insomnia | 3 (23%)
Hypomagnesemia | 2 (15%)
Procedural complications* | 2 (15%)
*Procedural complications included respiratory and cardiac arrest.

Other clinically significant adverse reaction includes worsening in duration and frequency of oculogyric crises during hospitalization following administration of KEBILIDI reported in one patient.

8 USE IN SPECIFIC POPULATIONS

8.1 Pregnancy

Risk Summary

There are no clinical data from the use of KEBILIDI in pregnant women. Animal reproductive and developmental toxicity studies have not been conducted with KEBILIDI.

In the US general population, the estimated background risk of major birth defects and miscarriage in clinically recognized pregnancies is 2% to 4% and 15% to 20%, respectively.

8.2 Lactation

Risk Summary

There is no data on the presence of KEBILIDI in human milk, the effects on the breastfed infant, or the effects on milk production.

8.3 Females and Males of Reproductive Potential

Pregnancy Testing

Pregnancy status of females with reproductive potential should be verified. Sexually active females of reproductive potential should have a negative pregnancy test before administering KEBILIDI.

Contraception

There are insufficient exposure data to provide a recommendation concerning duration of contraception following treatment with KEBILIDI.

Infertility

There is no data on the effects of KEBILIDI on fertility.

8.4 Pediatric Use

The safety and effectiveness of KEBILIDI have been established in pediatric patients. The use of KEBILIDI was evaluated in a single-arm, open-label study that enrolled 13 pediatric patients aged 16 months to 10 years who had achieved skull maturity [see Adverse Reactions (6) and Clinical Studies (14)].

The safety and effectiveness of KEBILIDI have not been studied in pediatric patients younger than 16 months.

8.5 Geriatric Use

KEBILIDI has not been studied in patients 65 years of age and older.

11 DESCRIPTION

KEBILIDI (eladocagene exuparvovec-tneq) is a gene therapy product that expresses the human aromatic L-amino acid decarboxylase enzyme (hAADC). It is a recombinant adeno-associated virus serotype 2 (rAAV2) based vector containing the complementary DNA of the human DDC gene under the control of the cytomegalovirus immediate-early promoter. Eladocagene exuparvovec-tneq is produced in human embryonic kidney cells by recombinant DNA technology.

KEBILIDI is a sterile suspension administered by bilateral intraputaminal infusion in one surgical session at two sites (anterior and posterior) per putamen. Each single-dose 2 mL vial contains 2.8×10^11 vg in an extractable volume of 0.5 mL of suspension. Each mL of suspension contains 5.6×10^11 vg. Patients will receive a total dose of 1.8×10^11 vg delivered as four 0.08 mL (0.45×10^11 vg) infusions (two per putamen).

KEBILIDI is provided in a single-dose 2 mL vial containing a clear to slightly opaque, colorless to faint white liquid, free of visible particulates following thaw from its frozen state. The excipients include potassium chloride (3 mM), sodium chloride (337 mM), potassium dihydrogen phosphate (2 mM), disodium hydrogen phosphate (8 mM), and poloxamer 188 (0.001%).

12 CLINICAL PHARMACOLOGY

12.1 Mechanism of Action

KEBILIDI is a recombinant adeno-associated virus serotype 2 (rAAV2) based gene therapy designed to deliver a copy of the DDC gene which encodes the AADC enzyme. Intraputaminal infusion of KEBILIDI results in AADC enzyme expression and subsequent production of dopamine in the putamen.

12.2 Pharmacodynamics

Homovanillic Acid in Cerebrospinal Fluid

In Study 1, homovanillic acid (HVA), a downstream metabolite of dopamine, in cerebrospinal fluid (CSF) was measured at baseline, Week 8, and Week 48 using a high-performance liquid chromatography with tandem mass spectrometry (HPLC-MS/MS). In all patients of Study 1, an increase in CSF HVA levels from baseline was observed at Week 8 and Week 48 (Table 4).

Table 4: HVA Levels in CSF (Study 1)

Timepoint | Observed Values (nmol/L) | Change from Baseline (nmol/L) | Percent Change from Baseline(%)
Baseline
N | 13 | - | -
Median (Min, Max) | 3.34 (1.00, 93.73) | - | -
Week 8
N | 12 | 12 | 12
Median (Min, Max) | 35.09 (15.09, 150.48) | 26.62 (12.49, 56.75) | 534.7 (57.4, 2810.0)
Week 48
N | 9 | 9 | 9
Median (Min, Max) | 29.16 (14.21, 125.84) | 24.7 (13.21, 58.02) | 773.1 (33.9, 3991.0)
Note: Lower limit of quantification (LLOQ) was 2 nmol/L, and values reported as <LLOQ were imputed as 0.5*LLOQ.
Abbreviations: CSF=cerebrospinal fluid; HVA=homovanillic acid; N=number of subjects;
Max=maximum; Min=minimum

^18F-DOPA Uptake in the Putamen

^18F-DOPA is a positron-emitting fluorine-labeled substrate of the AADC enzyme. Following administration of ^18F-DOPA, its uptake into the putamen assessed by positron emission tomography (PET) imaging reflects AADC enzyme activity of dopaminergic neurons in the putamen. In Study 1, ^18F DOPA uptake in the putamen was assessed at baseline and followed up at Week 8 in 12 out 13 patients and at Week 48 in 10 out 13 patients indicating increased AADC ^18F DOPA uptake in all assessed patients. The median (range) percent increase from baseline was 259% (65% to 620%) at Week 8 and 271% (25% to 760%) at Week 48.

12.3 Pharmacokinetics

Biodistribution (within the body) and Vector Shedding (excretion/secretion)

KEBILIDI vector DNA levels in various tissues and secretions were determined using a validated quantitative polymerase chain reaction (qPCR) assay.

Nonclinical data

Biodistribution of eladocagene exuparvovec-tneq was evaluated in rats at Days 7, 30, 90, and 180 after single-dose intraputaminal infusion at dose levels up to 7.5×10^9 vg/animal (21-fold higher than the recommended human dose based on relative brain weight). At Day 7, vector DNA was observed in the putamen, cerebellum, cerebrum, and spinal cord. Vector DNA levels declined from Day 7 to Day 90, with DNA levels primarily sustained in the putamen at Day 180.

Clinical data

Following administration of KEBILIDI at a total dose for each patient of 1.8×10^11 vg in Study 1, biodistribution and viral shedding in CSF, blood, and urine were evaluated in 13 patients. CSF was collected at Weeks 8 and 48, and blood and urine were collected from Day 3 up to Week 48. Five (38%) patients showed detectable vector DNA levels in blood at Day 3 ranging from 4.0×103 to 6.5×10^3 copies/mL, which became below the limit of detection (<3.1×10^3 copies/mL) by Week 3. No vector was detected in CSF or urine.

12.6 Immunogenicity

The observed incidence of anti-AAV2 antibodies is highly dependent on the sensitivity and specificity of the assay. Differences in assay methods preclude meaningful comparisons of the incidence of anti-AAV2 antibodies in the studies described below with the incidence of anti-AAV2 antibodies in other studies.

There is no clinical experience with KEBILIDI in patients with pre-existing anti-AAV2 neutralizing antibody at titers >1:1200.

In Study 1, anti-AAV2 total binding antibodies and anti-AAV2 neutralizing antibodies were assessed from Day 3 up to Week 48 following administration of KEBILIDI. In all patients (N=13), titers of total binding antibody and neutralizing antibody increased from Week 3 and remained elevated, as measured at Week 48 (N=9). The highest titers in each patient ranged from 1:800 to 1:204,800 for total binding antibodies and from 1:80 to 1:10,240 for neutralizing antibody. Because of the small sample size of Study 1, there is insufficient data to determine the effect of anti-AAV2 antibody on the pharmacokinetics, pharmacodynamics, safety, or effectiveness.

13 NONCLINICAL TOXICOLOGY

13.1 Carcinogenesis, Mutagenesis, Impairment of Fertility

Carcinogenicity, genotoxicity, and fertility studies have not been performed with KEBILIDI.

14 CLINICAL STUDIES

The efficacy of KEBILIDI was evaluated in one open-label, single arm study (Study 1; NCT04903288). The study enrolled pediatric patients with genetically confirmed, severe AADC deficiency who had achieved skull maturity assessed with neuroimaging. The main efficacy outcome measure was gross motor milestone achievement evaluated at week 48 and assessed using the Peabody Developmental Motor Scale, Second Edition (PDMS-2). Patients treated with KEBILIDI were compared to an external untreated natural history cohort of 43 pediatric patients with severe AADC deficiency who had at least one motor milestone assessment after 2 years of age.

A total of 13 patients received a single total dose of 1.8×10^11 vg of KEBILIDI given as four intraputaminal infusions in a single stereotactic neurosurgical procedure. The demographic characteristics of the population were as follows: the median age was 2.8 years (1.3 to 10.8 years), 7 patients (54%) were female, 10 patients (77%) were Asian, 2 patients (15%) were White, and 1 patient was of “other” race. Twelve of the 13 patients had the severe phenotype of AADC deficiency, defined as having no motor milestone achievement at baseline and no clinical response to standard of care therapies. The one remaining patient had a “variant” of the severe disease phenotype, with the ability to sit with assistance but with lack of head control.

Gross motor milestone achievement at Week 48 was assessed in 12 of the 13 patients treated in Study 1 (one patient dropped out of the study prior to Week 48).

Eight (67%) of the 12 treated patients achieved a new gross motor milestone at week 48: 3 patients achieved full head control, 2 patients achieved sitting with or without assistance, 2 patients achieved walking backwards and the patient with the “variant” severe phenotype was able to sit unassisted. The two patients who achieved walking backwards at week 48 were treated before 2 years of age. The four patients who were unable to achieve new gross motor milestones at week 48 were treated between the ages of 2.8 and 10.8 years. In comparison, none of the 43 untreated patients with the severe phenotype had documented motor milestone achievement at last assessment at a median age of 7.2 years (range 2 to 19 years).

16 HOW SUPPLIED/STORAGE AND HANDLING

How Supplied

KEBILIDI is supplied in a single-dose 2 mL vial containing sterile, clear to slightly opaque, colorless to faint white liquid free of visible particulates, following thaw from its frozen state. Each KEBILIDI (eladocagene exuparvovec-tneq) vial contains 2.8×10^11 vg of eladocagene exuparvovec-tneq in an extractable volume of 0.5 mL of suspension. Each mL of suspension contains a nominal concentration of 5.6×10^11 vg of eladocagene exuparvovec-tneq.

Package (carton): NDC Number 52856-601-01

Container (vial): NDC Number 52856-601-11

Storage and Handling

Store and transport frozen at ≤-65°C (-85°F). Keep the vial in the supplied carton.

Thaw KEBILIDI prior to administration. If not used immediately, store at room temperature (up to 25°C [77°F]) and use within 6 hours of starting product thaw [see Dosage and Administration (2.3)]. Do not refreeze vial once thawed.

17 PATIENT COUNSELING INFORMATION

Discuss the following with patients and caregivers:

- Administration: Inform patients/caregivers that KEBILIDI administration involves an infusion into the brain that is administered during the neurosurgical procedure [see Administration 2.4)].
- Procedural Complications: Inform patients/caregivers about the complications of the neurosurgical procedure required for administration of KEBILIDI, including respiratory and cardiac arrest, cerebrospinal fluid (CSF) leak, intracranial bleeding, neuroinflammation, acute infarction, and infection [see Warnings and Precautions (5.1)].
- Dyskinesia: Inform patients/caregivers that they may experience dyskinesia within 3 months after treatment with KEBILIDI. Symptoms of dyskinesia may include involuntary movements of face, arm, leg, or entire body which may present as fidgeting, writhing, wriggling, head bobbing or body swaying. Advise patients and caregivers to contact their healthcare provider if these symptoms occur [see Warnings and Precautions (5.2)].
- Vector Shedding: Inform patients/caregivers that temporary vector shedding of KEBILIDI may occur for 3 weeks after administration. Advise patients/caregivers on proper hand hygiene and appropriate handling of waste materials generated from dressings and/or any secretions (e.g., blood, nasal secretions, urine, stool, and CSF). Recommended procedures include storage of waste material in sealed bags prior to disposal and wearing gloves for dressings changes and waste disposal. Patients should not donate blood, organs, tissues, or cells for transplantation [see Pharmacokinetics (12.3)].

Manufactured by: PTC Therapeutics, Inc.
Warren, NJ 07059 USA
US License No. 2168